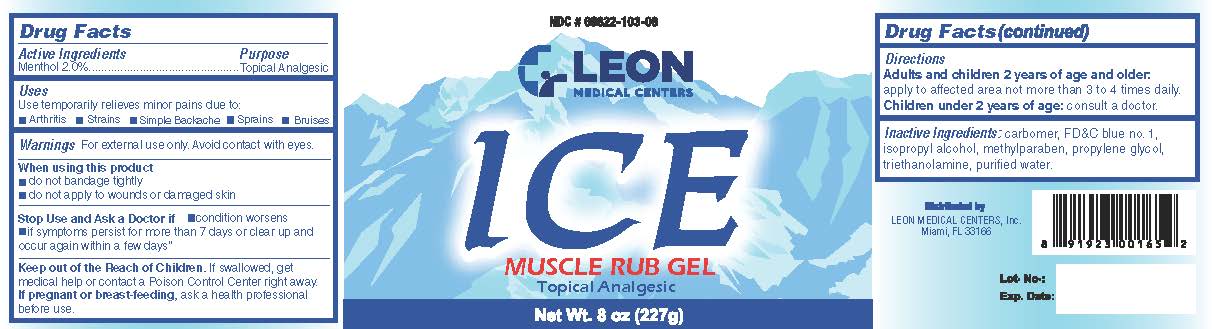 DRUG LABEL: ICE MUSCLE RUB Leon M.C
NDC: 69822-103 | Form: GEL
Manufacturer: Southern Sales & Service, Inc.
Category: otc | Type: HUMAN OTC DRUG LABEL
Date: 20231129

ACTIVE INGREDIENTS: MENTHOL 0.02 g/1 g
INACTIVE INGREDIENTS: FD&C BLUE NO. 1; ISOPROPYL ALCOHOL; METHYLPARABEN; PROPYLENE GLYCOL; TROLAMINE; WATER; CARBOMER HOMOPOLYMER, UNSPECIFIED TYPE

Leon Ice Muscle Rub

Active ingredients

Menthol 2.0%

Purpose

Topical Analgesic

Uses

Use temporarily relieves minor pains due to:

- Arthritis
- Strains
- Simple Backache
- Sprains
- Bruises

Warnings

For external use only. Avoid contact with eyes.

When using this product

- do not bandage tightly
- do not apply to wounds or damaged skin

Stop Use and Ask a Doctor if

- condition worsens
- if symptoms persist for more than 7 days or clear up and occur again within a few days"

Keep out of reach of children.

If swallowed, get medical help or contact a Poison Control Center right away.

If pregnant or breast-feeding,

ask a health professional before use.

Directions

apply to affected area not more than 3 to 4 times daily. Adults and children 2 years of age ad older:

consult a doctor. Children under 2 years of age:

Inactive Ingredients:

carbomer, FD&C Blue no. 1, isopropyl alcohol, methylparaben, propylene glycol, triethanolamine, purified water.